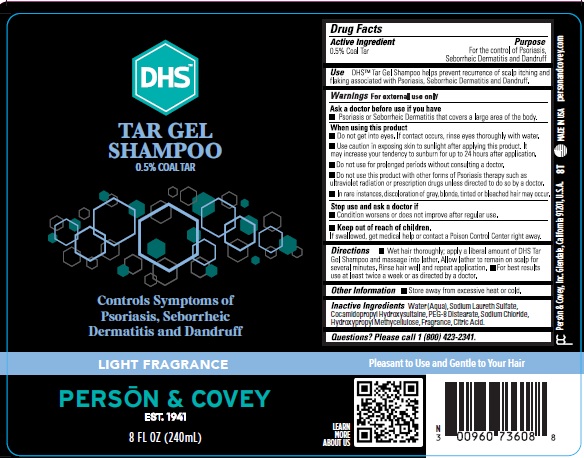 DRUG LABEL: DHS tar gel
NDC: 0096-0736 | Form: SHAMPOO
Manufacturer: Person and Covey
Category: otc | Type: HUMAN OTC DRUG LABEL
Date: 20251129

ACTIVE INGREDIENTS: COAL TAR 0.005 g/1 g
INACTIVE INGREDIENTS: TRIETHANOLAMINE LAURYL SULFATE; COCAMIDOPROPYL HYDROXYSULTAINE; SODIUM CHLORIDE; PEG-8 DISTEARATE; ANHYDROUS CITRIC ACID; HYPROMELLOSE 2910 (4000 MPA.S); WATER

DHS TAR GEL

Purpose

Controls symptoms of Psoriasis, Seborrheic Dermatitis and Dandruff.

Indications and use

Helps prevent recurrence of scalp itching and flaking associated with Psoriasis, Seborrheic Dermatitis and Dandruff.

Dosage and administration

Wet hair thoroughly, apply a liberal amount of shampoo and massage into lather. Allow lather to remain on scalp for several minutes. Rinse hair well and repeat application. For best results use at least twice a week or as directed by a physician.

OTC - ACTIVE INGREDIENT SECTION

Coal Tar

INACTIVE INGREDIENT SECTION

Purified Water

Triethanolamine Laurel Sulfite

Cocamidopropyl Hydroxysultaint

Sodium Chloride

PEG-8 Distearate

Hypromellose

Citric Acid

Keep out of the reach of children

Yes. If swallowed, get medical help or contact a Poison Control Center right away.

WARNINGS AND PRECAUTIONS SECTION

For external use only. Ask a physician before use if you have Psoriasis or Seborrheic Dermatitis that covers a large area of the body. Do not get into eyes. If contact occurs, rinse eyes thoroughly with water. Use caution in exposing skin to sunlight after applying this product. It may increase your tendency to sunburn for up to 24 hours after application. Do not use for prolonged periods without consulting a physician. Do not use this product with other forms of Psoriasis therapy such as ultraviolet radiation or prescription drugs, unless directed to do so by a physician. In rare instances, discoloration of gray, blond tinted or bleached hair may occur. Stop use and ask physician if condition worsens or does not improve after regular use. Store away from excessive heat or cold.